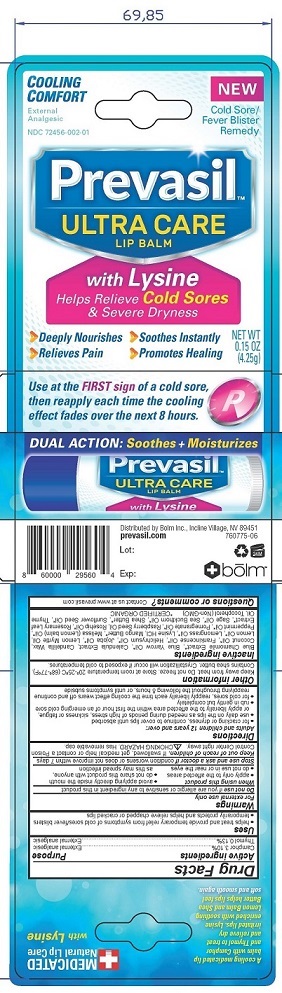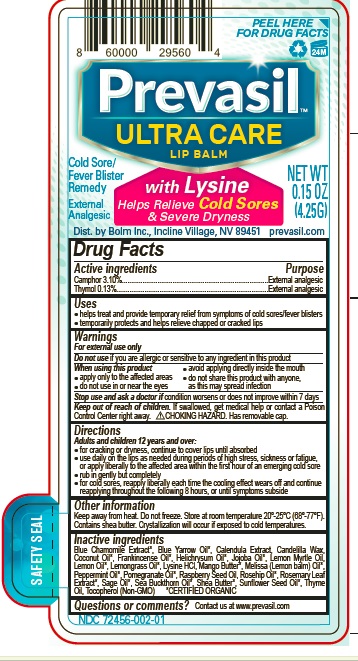 DRUG LABEL: Prevasil ULTRA CARE LIP BALM
NDC: 72456-002 | Form: STICK
Manufacturer: Bolm, Inc.
Category: otc | Type: HUMAN OTC DRUG LABEL
Date: 20190412

ACTIVE INGREDIENTS: CAMPHOR (SYNTHETIC) 31 mg/1 g; THYMOL 1.3 mg/1 g
INACTIVE INGREDIENTS: CHAMOMILE; ACHILLEA MILLEFOLIUM OIL; CALENDULA OFFICINALIS FLOWER; CANDELILLA WAX; COCONUT OIL; FRANKINCENSE OIL; HELICHRYSUM ITALICUM FLOWER OIL; JOJOBA OIL; BACKHOUSIA CITRIODORA LEAF OIL; LEMON OIL; EAST INDIAN LEMONGRASS OIL; LYSINE HYDROCHLORIDE; MANGIFERA INDICA SEED BUTTER; MELISSA OFFICINALIS LEAF OIL; PEPPERMINT OIL; POMEGRANATE SEED OIL; RASPBERRY SEED OIL; ROSA MOSCHATA OIL; ROSEMARY; SAGE OIL; HIPPOPHAE RHAMNOIDES SEED OIL; SHEA BUTTER; SUNFLOWER OIL; THYME OIL; TOCOPHEROL

Active ingredients

Camphor- 3.10% Thymol 0.13%

Purpose

External Analgesic

Warnings

For external use only
Do not use if you are allergic or sensitive to any ingredient in this product
When using this product
• apply only to the affected areas
• do not use in or near the eyes

• avoid applying directly inside the mouth

• do not share this product with anyone, as this may spread infection

Uses

• helps treat and provide temporary relief from symptoms of cold sores/fever blisters
• temporarily protects and helps relieve chapped or cracked lips

Stop use and ask a doctor if condition worsens or does not improve within 7 days

Keep out of reach of children. If swallowed, get medical help or contact a Poison
Control Center right away. CHOKING HAZARD. Has removable cap.

Directions

• for cracking or dryness, continue to cover lips until absorbed
• use daily on the lips as needed during periods of high stress, sickness or fatigue, or apply liberally to the affected area within the first hour of an emerging cold sore
• rub in gently but completely
• for cold sores/fever blisters, reapply liberally as the cooling effect wears off and continue reapplying throughout the following 8 hours, or until symptoms subside

Storage

- Keep away from heat. Do not freeze. Store at room temperature 20o-25oC (68o-77oF)

Inactive Ingredients

Blue Chamomile Extract*, Blue Yarrow Oil*, Calendula Extract, Candelilla Wax,
Coconut Oil*, Frankincense Oil*, Helichrysum Oil*, Jojoba Oil*, Lemon Myrtle Oil,
Lemon Oil*, Lemongrass Oil*, Lysine HCl, Mango Butter*, Melissa (Lemon balm)
Oil*, Peppermint Oil*, Pomegranate Oil*, Raspberry Seed Oil, Rosehip Oil*,
Rosemary Leaf Extract*, Sage Oil*, Sea Buckthorn Oil*, Shea Butter*, Sunflower
Seed Oil*, Thyme Oil, Tocopherol (Non-GMO) *CERTIFIED ORGANIC

Questions or comments?

Contact us at www.prevasil.com